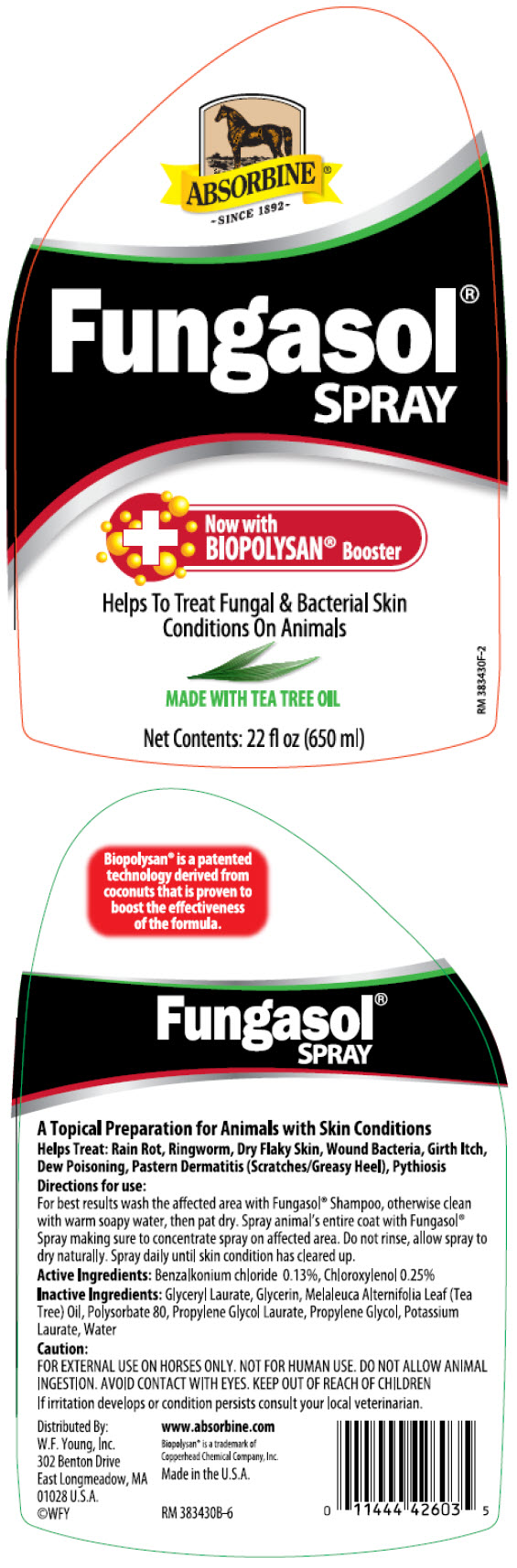 DRUG LABEL: Absorbine Fungasol
NDC: 11444-426 | Form: LIQUID
Manufacturer: W. F. Young, Inc.
Category: animal | Type: OTC ANIMAL DRUG LABEL
Date: 20210611

ACTIVE INGREDIENTS: CHLOROXYLENOL 0.25 g/100 mL; BENZALKONIUM CHLORIDE 0.13 g/100 mL

Fungasol®
SPRAY

Biopolysan® is a patented technology derived from coconuts that is proven to boost the effectiveness of the formula.

DESCRIPTION

A Topical Preparation for Animals with Skin Conditions

Helps Treat: Rain Rot, Ringworm, Dry Flaky Skin, Wound Bacteria, Girth Itch, Dew Poisoning, Pastern Dermatitis (Scratches/Greasy Heel), Pythiosis

Directions for use:

For best results wash the affected area with Fungasol® Shampoo, otherwise clean with warm soapy water, then pat dry. Spray animal's entire coat with Fungasol® Spray making sure to concentrate spray on affected area. Do not rinse, allow spray to dry naturally. Spray daily until skin condition has cleared up.

Active Ingredients: Benzalkonium chloride 0.13%, Chloroxylenol 0.25%

INACTIVE INGREDIENT

Inactive Ingredients: Glyceryl Laurate, Glycerin, Melaleuca Alternifolia Leaf (Tea Tree) Oil, Polysorbate 80, Propylene Glycol Laurate, Propylene Glycol, Potassium Laurate, Water

Caution:

FOR EXTERNAL USE ON HORSES ONLY. NOT FOR HUMAN USE.

DO NOT ALLOW ANIMAL INGESTION. AVOID CONTACT WITH EYES.

KEEP OUT OF REACH OF CHILDREN

If irritation develops or condition persists consult your local veterinarian.

Distributed By:
W.F. Young, Inc.
302 Benton Drive
East Longmeadow, MA
01028 U.S.A.
©WFY

www.absorbine.com

Biopolysan® is a trademark of
Copperhead Chemical Company, Inc.

Made in the U.S.A.

RM 383430

PRINCIPAL DISPLAY PANEL - 650 ml Bottle Label

ABSORBINE®
~SINCE 1892~

Fungasol®
SPRAY

Now with
BIOPOLYSAN® Booster

Helps To Treat Fungal & Bacterial Skin
Conditions On Animals

MADE WITH TEA TREE OIL

Net Contents: 22 fl oz (650 ml)

RM 383430F-2